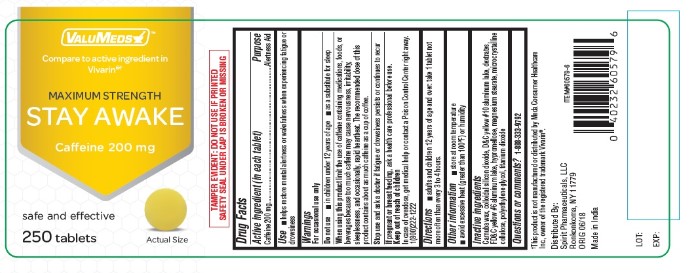 DRUG LABEL: Valumeds Maximum Strength Stay Awake
NDC: 68210-0403 | Form: TABLET
Manufacturer: Spirit Pharmaceuticals LLC
Category: otc | Type: HUMAN OTC DRUG LABEL
Date: 20231213

ACTIVE INGREDIENTS: CAFFEINE 200 mg/1 1
INACTIVE INGREDIENTS: CARNAUBA WAX; SILICON DIOXIDE; D&C YELLOW NO. 10; DEXTRATES; FD&C YELLOW NO. 6; MAGNESIUM STEARATE; MICROCRYSTALLINE CELLULOSE; POLYETHYLENE GLYCOL 400; TITANIUM DIOXIDE; HYPROMELLOSE, UNSPECIFIED

Valumeds Maximum Strength Stay Awake

Drug Facts

Active ingredient (in each tablet)
Caffeine 200 mg

Purpose

Alertness Aid

Use

■ helps restore mental alertness or wakefulness when experiencing fatigue or drowsiness

Warnings

For occasional use only

Do not use

■ in children under 12 years of age
■ as a substitute for sleep

When using this product limit the use of caffeine containing medications, foods, or beverages because too much caffeine may cause nervousness, irritability, sleeplessness, and occasionally, rapid heartbeat. The recommended dose of this product contains about as much caffeine as a cup of coffee.

Stop use and ask a doctor if fatigue or drowsiness persists or continues to recur

PREGNANCY OR BREAST FEEDING

If pregnant or breast-feeding, ask a health professional before use.

Keep out of reach of children.

OVERDOSAGE

In case of overdose, get medical help or contact a Poison Control Center right away.1(800)222-1222

Directions

■ adults and children 12 years of age and over: take 1 tablet not more often than every 3 to 4 hours.

Other information

■ store at room temperature
■ avoid excessive heat (greater than 100°F) or humidity

INACTIVE INGREDIENT

Carnuba wax, colloidal silicon dioxide, D&C yellow #10 aluminum lake, dextrates,
FD&C yellow #6 aluminum lake, hypromellose, magnesium stearate, microcrystalline
cellulose, polyethylene glycol, titanium dioxide

Questions or comments?

1-888-333-9792

PACKAGE LABEL

VALUMEDS

MAXIMUM STRENGTH
STAY AWAKE

Caffeine 200 mg

safe and effective

250 tablets